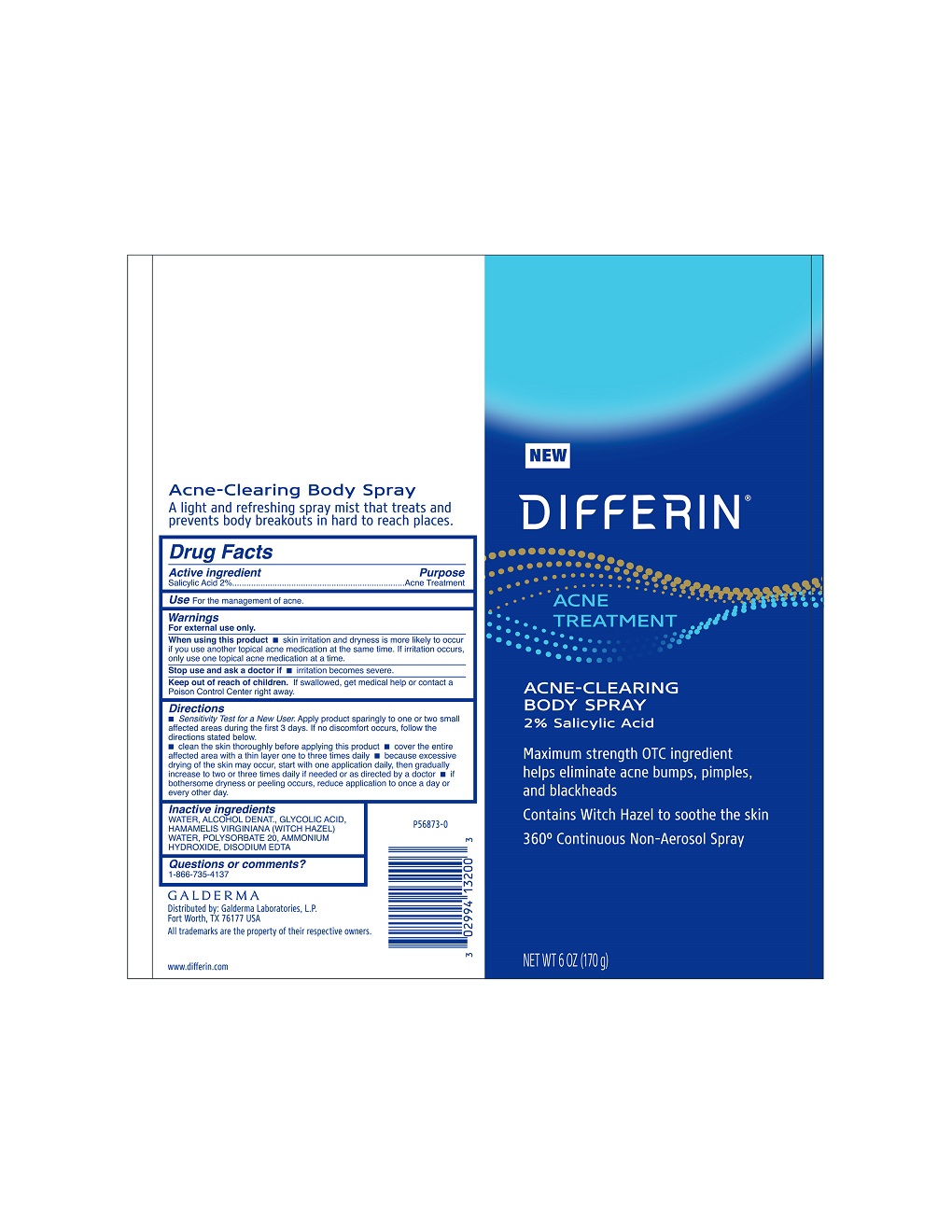 DRUG LABEL: Differin Acne Clearing Body
NDC: 0299-4132 | Form: AEROSOL, SPRAY
Manufacturer: Galderma Laboratories, L.P.
Category: otc | Type: HUMAN OTC DRUG LABEL
Date: 20231211

ACTIVE INGREDIENTS: Salicylic Acid 2 g/100 g
INACTIVE INGREDIENTS: Water; Alcohol; Glycolic Acid; Hamamelis Virginiana Top Water; Polysorbate 20; Ammonia; Edetate Disodium Anhydrous

Drug Facts

Active Ingredient

Salicylic Acid 2%

Purpose

Acne Treatment

Use

For the management of acne

Warnings

For external use only

When using this product

• skin irritation and dryness is more likely to occur if you use another topical acne medication at the same time. If irritation occurs, only use one topical acne medication at a time.

Stop use and ask a doctor if

• irritation becomes severe.

Keep out of reach of children.

If swallowed, get medical help or contact a Poison Control Center right away.

Directions

• Sensitivity Test for a New User. Apply product sparingly to one or two small affected areas during the first 3 days. If no discomfort occurs, follow the directions stated below. • clean the skin thoroughly before applying this product • cover the entire affected area with a thin layer one to three times daily • because excessive drying of the skin may occur, start with one application daily, then gradually increase to two or three times daily if needed or as directed by a doctor • if bothersome dryness or peeling occurs, reduce application to once a day or every other day.

Inactive Ingredients

Water, Alcohol Denat., Glycolic Acid, Hamamelis Virginiana (Witch Hazel) Water, Polysorbate 20, Ammonium Hydroxide, Disodium EDTA

Questions or comments? 1-866-735-4137

Distributed by: Galderma Laboratories, L.P.,
Fort Worth, TX 76177 USA
All trademarks are the property of their respective owners.
www.differin.com
P56873-0

PRINCIPAL DISPLAY PANEL - 6 OZ bottle

NEW
DIFFERIN®
ACNE
TREATMENT

ACNE - CLEARING
BODY SPRAY

2% Salicylic Acid

Maximum strength OTC ingredient
helps eliminate acne bumps, pimples,
and blackheads

Contains Witch Hazel to soothe the skin
360° Continuous Non-Aerosol Spray

NET WT 6 OZ (170 g)